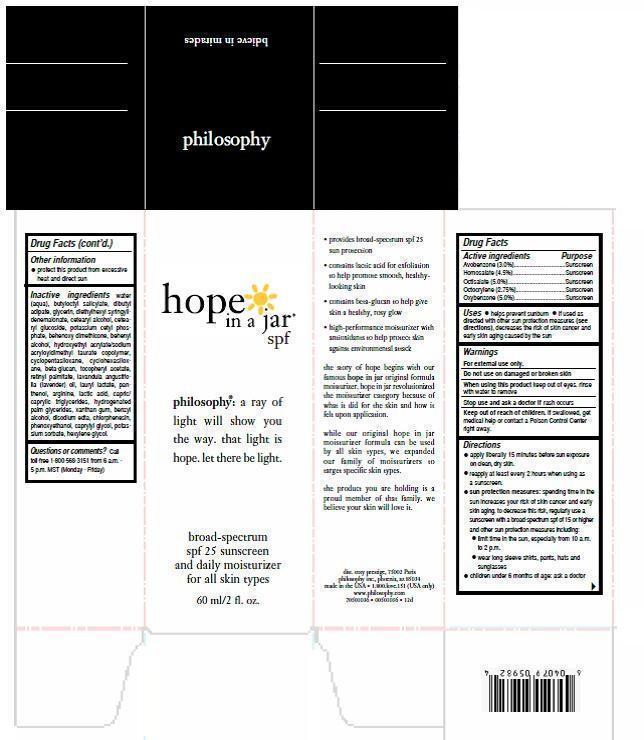 DRUG LABEL: hope in a jar
NDC: 50184-1032 | Form: CREAM
Manufacturer: Philosophy
Category: otc | Type: HUMAN OTC DRUG LABEL
Date: 20130417

ACTIVE INGREDIENTS: Avobenzone 2.088 g/60 mL; HOMOSALATE 2.838 g/60 mL; OCTISALATE 3.041 g/60 mL; OCTOCRYLENE 1.733 g/60 mL; OXYBENZONE 3.96 g/60 mL
INACTIVE INGREDIENTS: Water; BUTYLOCTYL SALICYLATE; DIBUTYL ADIPATE; GLYCERIN; DIETHYLHEXYL SYRINGYLIDENEMALONATE; CETEARYL GLUCOSIDE; POTASSIUM CETYL PHOSPHATE; HYDROXYETHYL ACRYLATE/SODIUM ACRYLOYLDIMETHYL TAURATE COPOLYMER (45000 MPA.S AT 1%); CYCLOMETHICONE 5; CYCLOMETHICONE 6; .ALPHA.-TOCOPHEROL ACETATE; VITAMIN A PALMITATE; LAVENDER OIL; LAURYL LACTATE; PANTHENOL; ARGININE; LACTIC ACID; TRICAPRIN; HYDROGENATED PALM GLYCERIDES; XANTHAN GUM; BENZYL ALCOHOL; EDETATE DISODIUM; POLYSORBATE 60; SORBITAN ISOSTEARATE; CHLORPHENESIN; PHENOXYETHANOL; CAPRYLYL GLYCOL; POTASSIUM SORBATE; HEXYLENE GLYCOL

Active Ingredients

Avobenzone 3.0%

Homosalate 4.5%

Octislate 5.0%

Octocrylene 2.75%

Oxybenzone 5.0%

Purpose

Sunscreen

Keep out of reach of children.

If swallowed, get medical help or contact a Poison Control Center right away.

Uses

- helps prevent sunburn
- if used as directed with other sun protection measures (see Directions), decreases the risk of skin cancer and early skin aging caused by the sun

Warnings

For external use only.

Do not use on damage or broken skin.

When using this product keep out of eyes.

Rinse with water to remove.

Stop use and ask a doctor if rash occurs.

Keep out of reach of children. If swallowed, get medical help or contact a Poison Control Center right away.

Directions

- apply liberally 15 minutes before sun exposure
- reapply at least ever 2 hours
- use a water resistant sunscreen if swimming or sweating
- Sun Protection Measures. Spending time in the sun increases your risk of skin cancer and early skin aging. To decrease this risk, regulalry use a sunscreen with broad spectrum SPF of 15 or higher and other sun protection measures, including:
- limit time in the sun, especially from 10 a.m.-2p.m.
- wear long-sleeve shirts, pants, hats and sunglasses
- children under 6 months: ask a doctor--this product should NOT be sued on children of any age

Inactive Ingredients

water, butyloctyl salicylate, dibutyl adipate, glycerin, diethylhexyl syringlidenemalonate, cetearyl alcohol, cetearyl glucoside, potassium cetyl phosphate, behenoxy dimethicone, behenyl alcohol, hydroxyethnyl acrylate/sodium acryloyldimethyl taurate copolymer, cyclopentasiloxane, cyclohexasiloxane, beta-glucan, tocopheryl acetate, retinyl palmitate, lavandula angustifolia (lavendar oil), lauryl lactate, panthenol, arginine, lactic acid, capric/caprylic triglyceride, hydrogenated palm glycerides, xanthan gum, benzyl alcohl, disodium edta, polysorbate 60, sorbitan isostearate, chlorphenesin, phenoxyethanol, caprylyl glycol, potassium sorbate, hexylene glycol.

Other Information

- protect this product from excessive heat and direct sun

Questions or Comments?

Call toll free 1-800-568-3151 from 6 a.m.-5 p.m. MST (Monday-Friday)